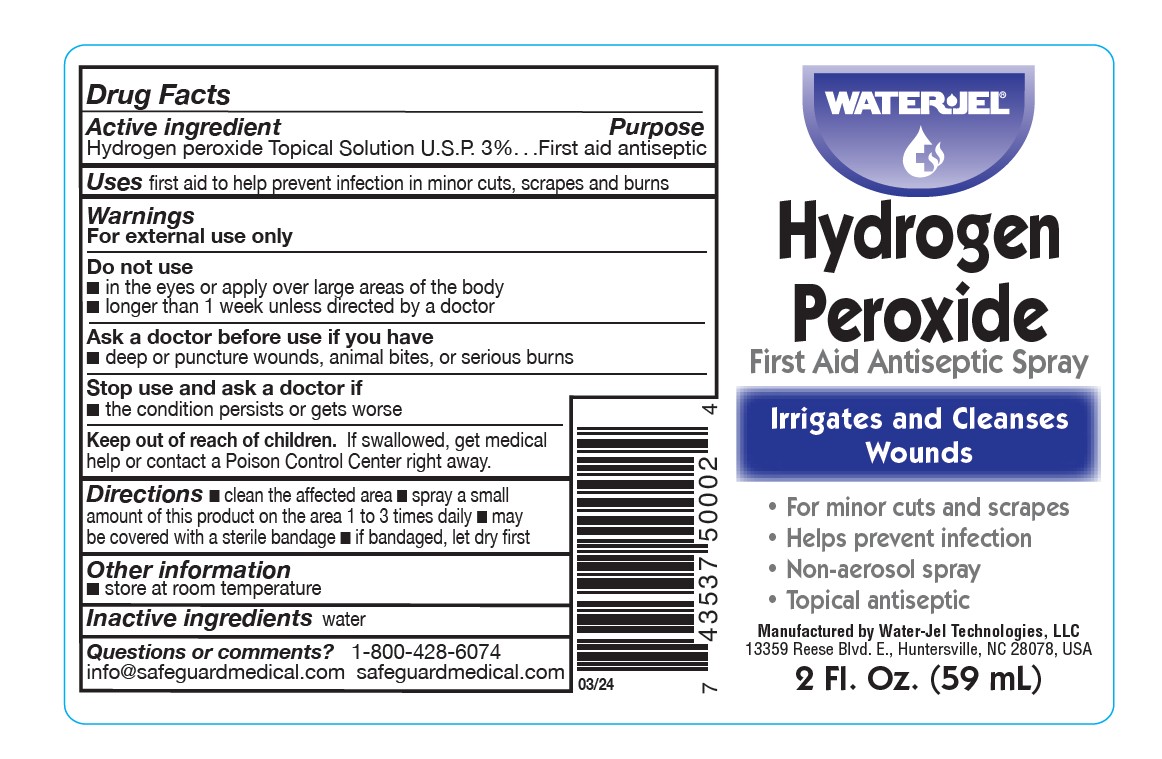 DRUG LABEL: Water Jel Hydrogen Peroxide
NDC: 59898-403 | Form: SPRAY
Manufacturer: Water-Jel Technologies
Category: otc | Type: HUMAN OTC DRUG LABEL
Date: 20251231

ACTIVE INGREDIENTS: HYDROGEN PEROXIDE 3 mL/100 mL
INACTIVE INGREDIENTS: WATER

Hydrogen Peroxide

Active ingredient

Hydrogen peroxide Topical Solution U.S.P 3%

Purpose

First aid antiseptic

Uses

first aid to help prevent infection in minor cuts, scrapes and burns

Warnings

For external use only

Do not use

- in the eyes or apply over large areas of the body
- longer than 1 week unless directed by a doctor

Ask a doctor before use if you have

- deep or puncture wounds, animal bites, or serious burns

Stop use and ask a doctor if

- the condition persists or gets worse

Keep out of reach of children

If swallowed, get medical help or contact a Poison Control Center right away.

Directions

- clean the affected area
- spray a small amount of this product on the area 1 to 3 times daily
- may be covered with a sterile bandage
- if bandaged, let dry first

Other information

- store at room temperature

Inactive ingredients

water

Questions or comments?

855-428-6074

safeguardmedical.com

Manufactured by Water-Jel Technologies, LLC

13359 Reese Blvd. E, Huntersville, NC 28078